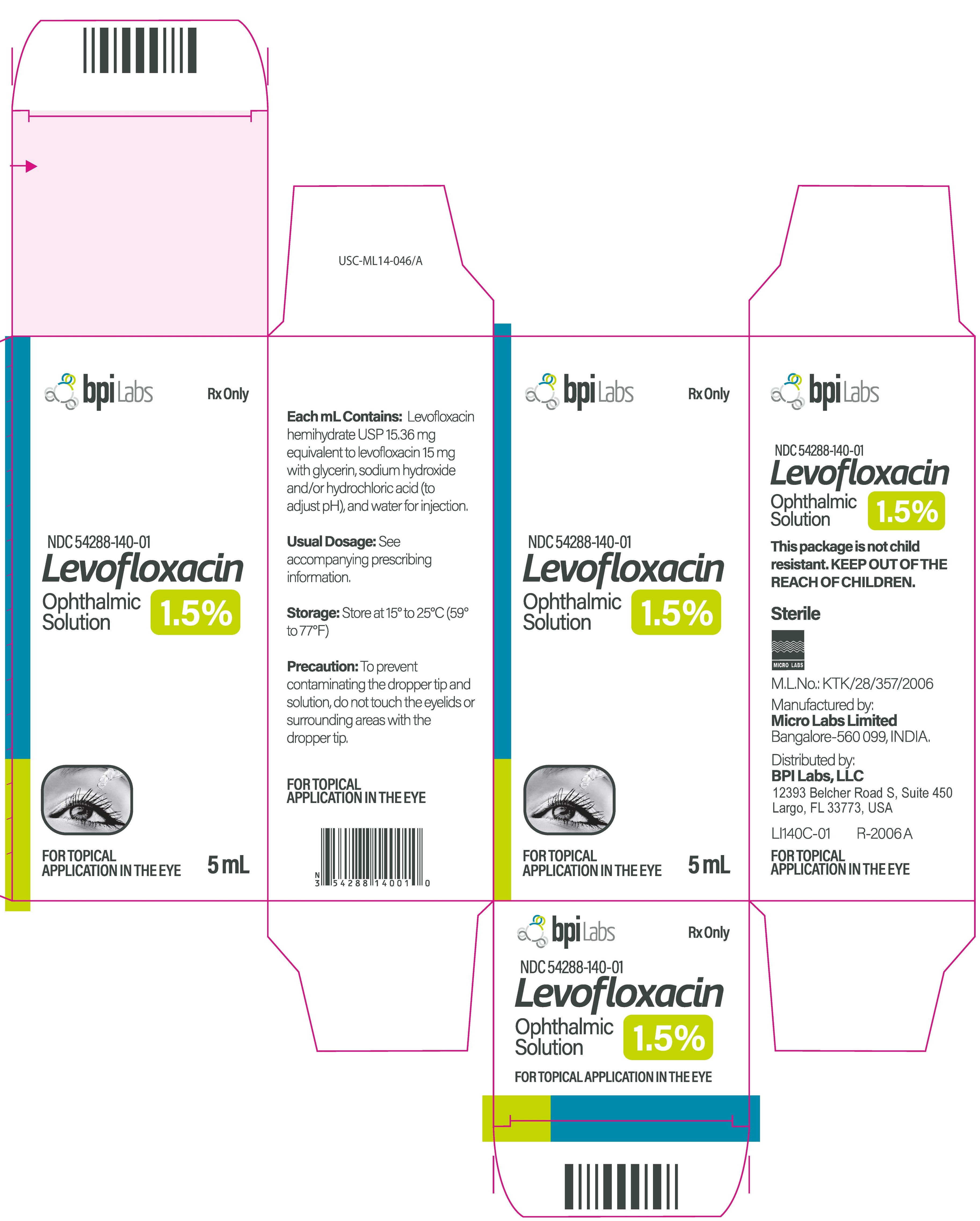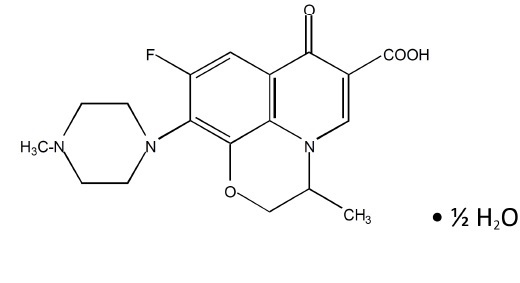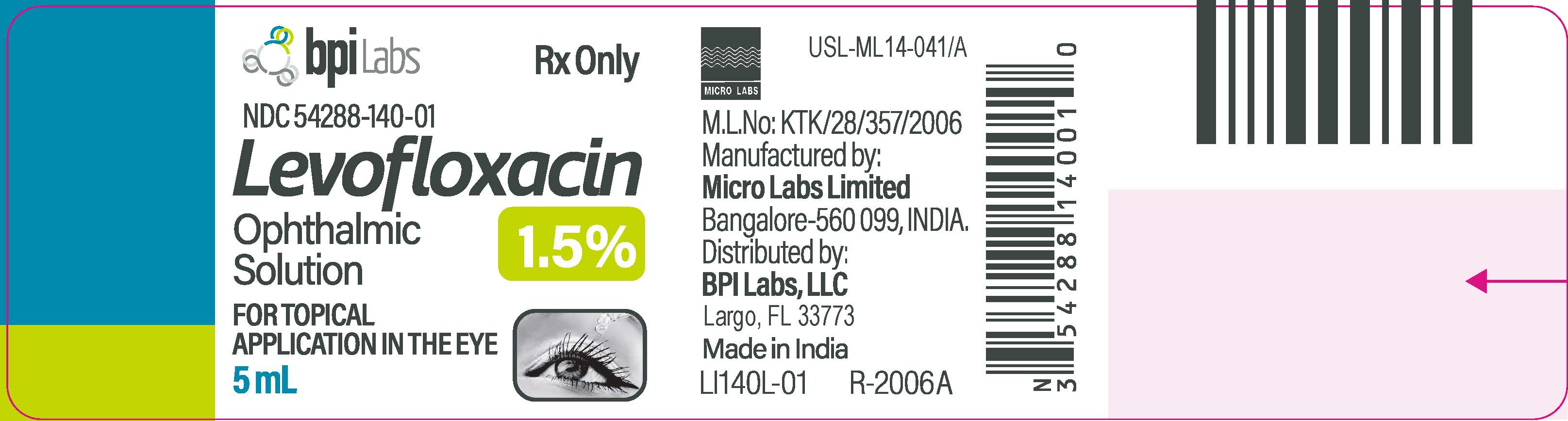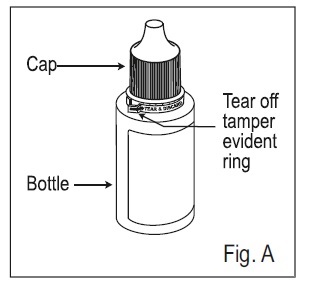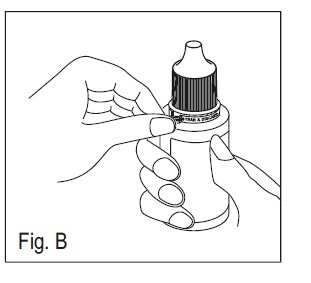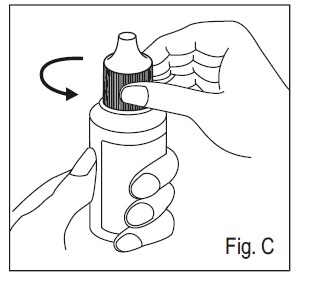 DRUG LABEL: Levofloxacin
NDC: 54288-140 | Form: SOLUTION/ DROPS
Manufacturer: BPI LABS LLC
Category: prescription | Type: HUMAN PRESCRIPTION DRUG LABEL
Date: 20251226

ACTIVE INGREDIENTS: LEVOFLOXACIN 15 mg/1 mL
INACTIVE INGREDIENTS: GLYCERIN; HYDROCHLORIC ACID; SODIUM HYDROXIDE; WATER

HIGHLIGHTS OF PRESCRIBING INFORMATION

These highlights do not include all the information needed to use LEVOFLOXACIN OPHTHALMIC SOLUTION safely and effectively. See full prescribing information for LEVOFLOXACIN OPHTHALMIC SOLUTION.
LEVOFLOXACIN ophthalmic solution 1.5%, sterile topical ophthalmic solution
Initial U.S. Approval: 1996

1 INDICATIONS AND USAGE

Levofloxacin ophthalmic solution is a topical quinolone anti-microbial indicated for the treatment of corneal ulcer caused by susceptible strains of the following bacteria:

Corynebacterium species *

Staphylococcus aureus

Staphylococcus epidermidis

Streptococcus pneumonia

Viridans group streptococci*

Pseudomonas aeruginosa

Serratia marcescens*

*Efficacy for this organism was studied in fewer than 10 infections. (1)

2 DOSAGE AND ADMINISTRATION

Days 1 through 3:

Instill one to two drops in the affected eye(s) every 30 minutes to 2 hours while awake and approximately 4 and 6 hours after retiring.

Day 4 through treatment completion:

Instill one to two drops in the affected eye(s) every 1 to 4 hours while awake. (2)

3 DOSAGE FORMS AND STRENGTHS

5 cc container filled with 5 mL sterile ophthalmic solution of levofloxacin, 1.5% (3)

4 CONTRAINDICATIONS

Levofloxacin ophthalmic solution is contraindicated in patients with a history of hypersensitivity to levofloxacin, to other quinolones, or to any of the components in this medication. (4)

5 WARNINGS AND PRECAUTIONS

- Hypersensitivity and anaphylaxis have been reported with systemic use of levofloxacin. (5.1)
- Prolonged use may result in the overgrowth of non- susceptible organisms, including fungi. (5.2)
- Patients should not wear contact lenses if they have signs or symptoms of corneal ulcer. (5.3)

6 ADVERSE REACTIONS

The most frequently reported adverse reactions in the overall study population were headache and a taste disturbance following instillation. These reactions occurred in approximately 8 to 10% of patients. (6)

To report SUSPECTED ADVERSE REACTIONS,contact BPI Labs LLC at (727)471-0850 or FDA at 1-800-FDA-1088 or www.fda.gov/medwatch.

FULL PRESCRIBING INFORMATION

1 INDICATIONS AND USAGE

Levofloxacin ophthalmic solution is indicated for the treatment of corneal ulcer caused by susceptible strains of the following bacteria:

Gram-positive bacteria:

Corynebacterium species

Staphylococcus aureus

Staphylococcus epidermidis

Streptococcus pneumonia

Viridans group streptococci*

Gram-negative bacteria:

Pseudomonas aeruginosa

Serratia marcescens*

*Efficacy for this organism was studied in fewer than 10 infections

2 DOSAGE AND ADMINISTRATION

Days 1 through 3:

Instill one to two drops in the affected eye(s) every 30 minutes to 2 hours while awake and approximately 4 and 6 hours after retiring.

Day 4 through treatment completion:

Instill one to two drops in the affected eye(s) every 1 to 4 hours while awake.

3 DOSAGE FORMS AND STRENGTHS

5 cc bottle filled with 5 mL sterile ophthalmic solution of levofloxacin, 1.5%.

4 CONTRAINDICATIONS

Levofloxacin ophthalmic solution is contraindicated in patients with a history of hypersensitivity to levofloxacin, to other quinolones, or to any of the components in this medication.

5 WARNINGS AND PRECAUTIONS

5.1 Hypersensitivity Reactions

In patients receiving systemically administered quinolones, including levofloxacin, serious and occasionally fatal hypersensitivity (anaphylactic) reactions have been reported, some following the first dose. Some reactions were accompanied by cardiovascular collapse, loss of consciousness, angioedema, (including laryngeal, pharyngeal or facial edema), airway obstruction, dyspnea, urticaria and itching. If an allergic reaction to levofloxacin occurs, discontinue the drug. Serious acute hypersensitivity reactions may require immediate emergency treatment. Oxygen and airway management should be administered as clinically indicated.

5.2 Growth of Resistant Organisms with Prolonged Use

As with other anti-infectives, prolonged use may result in overgrowth of non-susceptible organisms, including fungi. If superinfection occurs, discontinue use and institute alternative therapy. Whenever clinical judgment dictates, the patient should be examined with the aid of magnification, such as slit-lamp biomicroscopy, and where appropriate, fluorescein staining.

5.3 Avoidance of Contact Lens Wear

Patients should be advised not to wear contact lenses if they have signs and symptoms of corneal ulcer.

6 ADVERSE REACTIONS

The most frequently reported adverse reactions in the overall study population were headache and a taste disturbance following instillation. These reactions occurred in approximately 8 to 10% of patients. Adverse reactions occurring in approximately 1 to 2% of patients included decreased/blurred vision, diarrhea, dyspepsia, fever, infection, instillation site irritation/discomfort, ocular infection, nausea, ocular pain/discomfort, and throat irritation. Other reported ocular reactions occurring in less than 1% of patients included chemosis, corneal erosion, diplopia, floaters, hyperemia, lid edema, and lid erythema.

8 USE IN SPECIFIC POPULATIONS

8.1 Pregnancy

Pregnancy Category C

Teratogenic Effects: Levofloxacin at oral doses of 810 mg/kg/day in rats caused decreased fetal body weight and increased fetal mortality. No teratogenic effect was observed when rabbits were dosed orally as high as 50 mg/kg/day, at which systemic exposure was estimated to be 250 times that observed at the maximum recommended human ophthalmic dose, or when dosed intravenously as high as 25 mg/kg/day, at which systemic exposure was estimated to be 120 times that observed at the maximum recommended human ophthalmic dose.

There are, however, no adequate and well-controlled studies in pregnant women. Levofloxacin should be used during pregnancy only if the potential benefit justifies the potential risk to the fetus.

8.3 Nursing Mothers

Levofloxacin has not been measured in human milk. Based on data from ofloxacin, it can be presumed that levofloxacin is excreted in human milk. Caution should be exercised when levofloxacin is administered to a nursing mother.

8.4 Pediatric Use

Safety and effectiveness in children below the age of six years have not been established. Oral administration of systemic quinolones has been shown to cause arthropathy in immature animals. There is no evidence that the ophthalmic administration of levofloxacin has any effect on weight bearing joints.

8.5 Geriatric Use

No overall differences in safety or effectiveness have been observed between elderly and other adult patients.

11 DESCRIPTION

Levofloxacin ophthalmic solution 1.5% is a sterile topical ophthalmic solution. Levofloxacin is a fluoroquinolone antibacterial active against a broad spectrum of Gram-positive and Gram-negative ocular pathogens. Levofloxacin is a fluorinated 4-quinolone containing a six-member (pyridobenzoxazine) ring from positions 1 to 8 of the basic ring structure. Levofloxacin is the pure (-)-(S)-enantiomer of the racemic drug substance, ofloxacin. It is more soluble in water at neutral pH than ofloxacin.

C18H20FN3O4 ·½ H2O Mol Wt 370.38

Chemical Name: (-)-(S)-9-fluoro-2,3-dihydro-3-methyl-10-(4-methyl-1-piperazinyl)-7-oxo-7 H- pyrido[1,2,3- de]-1,4 benzoxazine-6-carboxylic acid hemihydrate. Levofloxacin (hemihydrate) USP is a yellowish-white crystalline powder. Each mL of levofloxacin ophthalmic solution contains 15.36 mg of levofloxacin hemihydrate USP equivalent to 15 mg levofloxacin.

Contains: Active: Levofloxacin (hemihydrate) USP is a light yellowish-white; Inactives: glycerin and water for injection. May also contain hydrochloric acid and/or sodium hydroxide to adjust pH to approximately 6.7. Levofloxacin ophthalmic solution is isotonic with an osmolality of approximately 291 mOsm/kg.

12 CLINICAL PHARMACOLOGY

12.1 Mechanism of Action

Levofloxacin is a member of the fluoroquinolone class of anti-microbial drug (See 12.4 Microbiology).

12.2 Pharmacokinetics

Levofloxacin concentration in plasma was measured in 14 healthy adult volunteers during a 16-day course of treatment with levofloxacin ophthalmic solution. The dosing schedule was 1 to 2 drops per eye once in the morning on Days 1 and 16; 1 to 2 drops per eye every two hours Days 2 through 8; and 1 to 2 drops per eye every four hours Days 9 through 15. The mean levofloxacin concentration in plasma 1 hour post dose ranged from 3.13 ng/mL on Day 1 to 10.4 ng/mL on Day 16.

Maximum mean levofloxacin concentrations increased from 3.22 ng/mL on Day 1 to 10.9 ng/mL on Day 16, which is more than 400 times lower than those reported after standard oral doses of levofloxacin.

Levofloxacin concentration in tears was measured in 100 healthy adult volunteers at various time points following instillation of 2 drops of levofloxacin ophthalmic solution. Mean tear concentration measured 15 minutes after instillation was 757 mcg/mL.

12.4 Microbiology

Levofloxacin is the L-isomer of the racemate, ofloxacin, a quinolone antimicrobial agent. The antibacterial activity of ofloxacin resides primarily in the L-isomer. The mechanism of action of levofloxacin and other fluoroquinolone antimicrobials involves the inhibition of bacterial topoisomerase IV and DNA gyrase (both of which are type II topoisomerases), enzymes required for DNA replication, transcription, repair, and recombination.

Levofloxacin has in vitro activity against a wide range of Gram-negative and Gram-positive microorganisms and is often bactericidal at concentrations equal to or slightly greater than inhibitory concentrations.

Fluoroquinolones, including levofloxacin, differ in chemical structure and mode of action from ß-lactam antibiotics and aminoglycosides, and therefore may be active against bacteria resistant to ß-lactam antibiotics and aminoglycosides. Additionally, ß-lactam antibiotics and aminoglycosides may be active against bacteria resistant to levofloxacin. Resistance to levofloxacin due to spontaneous mutation in vitro is a rare occurrence (range: 10^(- 9) to 10^(- 10)).

Levofloxacin has been shown to be active against most strains of the following microorganisms, both in vitro and in clinical infections as described in the INDICATIONS AND USAGE section.

Aerobic gram-positive microorganisms:

Corynebacterium species*

Staphylococcus aureus

Staphylococcus epidermidis

Streptococcus pneumoniae

Viridans group streptococci*

Aerobic gram-negative microorganisms:

Pseudomonas aeruginosa

Serratia marcescens*

*Efficacy for this organism was studied in fewer than 10 infections.

The following in vitro data are also available, but their clinical significance in ophthalmic infections is unknown. The safety and effectiveness of levofloxacin in treating ophthalmological infections due to these microorganisms have not been established in adequate and well controlled trials.

These organisms are considered susceptible when evaluated using systemic breakpoints. However, a correlation between the in vitro systemic breakpoint and ophthalmological efficacy has not been established. The list of organisms is provided as guidance only in assessing the potential treatment of corneal ulcer. Levofloxacin exhibits in vitro minimal inhibitory concentrations (MICs) of 2 mcg/mL or less (systemic susceptible breakpoint) against most (≥ 90%) strains of the following ocular pathogens:

Aerobic gram-positive microorganisms:

Enterococcus faecalis (many strains are only moderately susceptible)

Staphylococcus saprophyticus

Streptococcus agalactiae

Streptococcus pyogenes

Streptococcus (Group C/F)

Streptococcus (Group G)

Aerobic gram-negative microorganisms:

Acinetobacter baumannii

Acinetobacter lwoffii

Citrobacter koseri

Citrobacter freundii

Enterobacter aerogenes

Enterobacter cloacae

Escherichia coli

Haemophilus influenzae

Haemophilus parainfluenzae

Klebsiella oxytoca

Klebsiella pneumonia

Legionella pneumophila

Moraxella catarrhalis

Morganella morganii

Neisseria gonorrhoeae

Pantoea agglomerans

Proteus mirabilis

Proteus vulgaris

Providencia rettgeri

Providencia stuartii

Pseudomonas fluorescens

13 NONCLINICAL TOXICOLOGY

13.1 Carcinogenesis, Mutagenesis, Impairment of Fertility

In a long term carcinogenicity study in rats, levofloxacin exhibited no carcinogenic or tumorigenic potential following daily dietary administration for 2 years at doses up to 100 mg/kg/day, corresponding to plasma levels that were 245 times maximum clinical exposure, based on C max.

Levofloxacin was not mutagenic in the following assays: Ames bacterial mutation assay (S. typhimurium and E. coli) CHO/HGPRT forward mutation assay, mouse micronucleus test, mouse dominant lethal test, rat unscheduled DNA synthesis assay, and the in vivo mouse sister chromatid exchange assay. It was positive in the in vitro chromosomal aberration (CHL cell line) and in vitro sister chromatid exchange (CHL/IU cell line) assays. Levofloxacin caused no impairment of fertility or reproduction in rats at oral doses as high as 360 mg/kg/day, at which systemic exposure was estimated to be 2,600 times that at the maximum recommended human ophthalmic dose.

14 CLINICAL STUDIES

In two randomized, double-masked, multi-center, controlled clinical trials of 280 patients with positive cultures, subjects were dosed with levofloxacin or ofloxacin 0.3% ophthalmic solution.

Dosing occurred on Days 1 through 3 every two hours while awake and 4 and 6 hours after retiring. Dosing occurred on Day 4 through treatment completion 4 times daily while awake. Clinical cure was defined as complete re-epithelialization and no progression of the infiltrate for two consecutive visits. The levofloxacin treated subjects had an approximately equal mean clinical cure rate of 80% (73% to 87%) compared to 84% (82% to 86%) for the subjects treated with ofloxacin 0.3% ophthalmic solution.

16 HOW SUPPLIED/STORAGE HANDLING

Levofloxacin ophthalmic solution 1.5% is supplied in a sterile with a white opaque cylindrical shaped low density polyethylene bottle with an open white opaque cone shaped low density polyethylene controlled dropper tip and a tan color cone shaped high density polyethylene cap in the following size:

5 mL fill in 5 cc container– NDC 54288-140-01

Storage: Store at 15° to 25°C (59° to 77°F).

17 PATIENT COUNSELING INFORMATION

17.1 Avoid Contamination of the Product

Advise patients to avoid contaminating the applicator tip with material from the eye, finger, or other source.

17.2 Avoid Contact Lens Wear

Advise patients not to wear contact lenses if they have signs and symptoms of corneal ulcer.

17.3 Hypersensitivity Reactions

Systemically administered quinolones, including levofloxacin, have been associated with hypersensitivity reactions, even following a single dose. Advise patients to discontinue use immediately and contact their physician at the first sign of a rash or allergic reactions.

INSTRUCTIONS FOR USE

Before you use Levofloxacin Ophthalmic Solution for the first time:

1. Check to make sure that the tamper evident ring between the bottle and the cap is not broken (See Figure A). If the tamper evident ring is broken or missing, contact your pharmacist.

2. Tear off the tamper evident ring (See Figure B).

3. To open the bottle, remove the cap by turning it in the counterclockwise direction (See Figure C).

This Instructions for Use has been approved by the U.S. Food and Drug Administration.

Manufactured by:

Micro Labs Limited

Bangalore-560099. INDIA.

Distributed by:

BPI Labs, LLC

12393 Belcher Road S, Suite 450

Largo, FL 33773, USA

LI32I R-2006A

PACKAGE LABEL.PRINCIPAL DISPLAY PANEL

NDC 54288-140-01
Levofloxacin Ophthalmic Solution 1.5%
FOR TOPICAL APPLICATION IN THE EYE
Rx Only
5 mL
BPI LABS, LLC

Rx Only NDC 54288-140-01
Levofloxacin Ophthalmic Solution 1.5%
FOR TOPICAL APPLICATION IN THE EYE
5 mL
BPI LABS, LLC